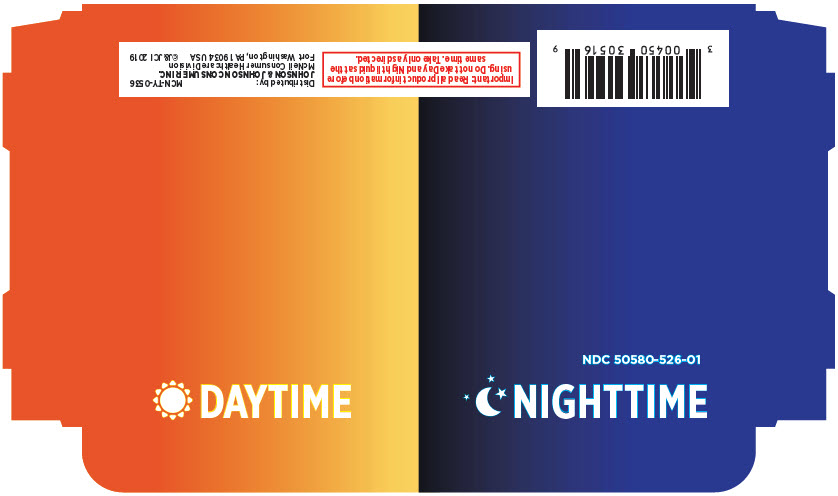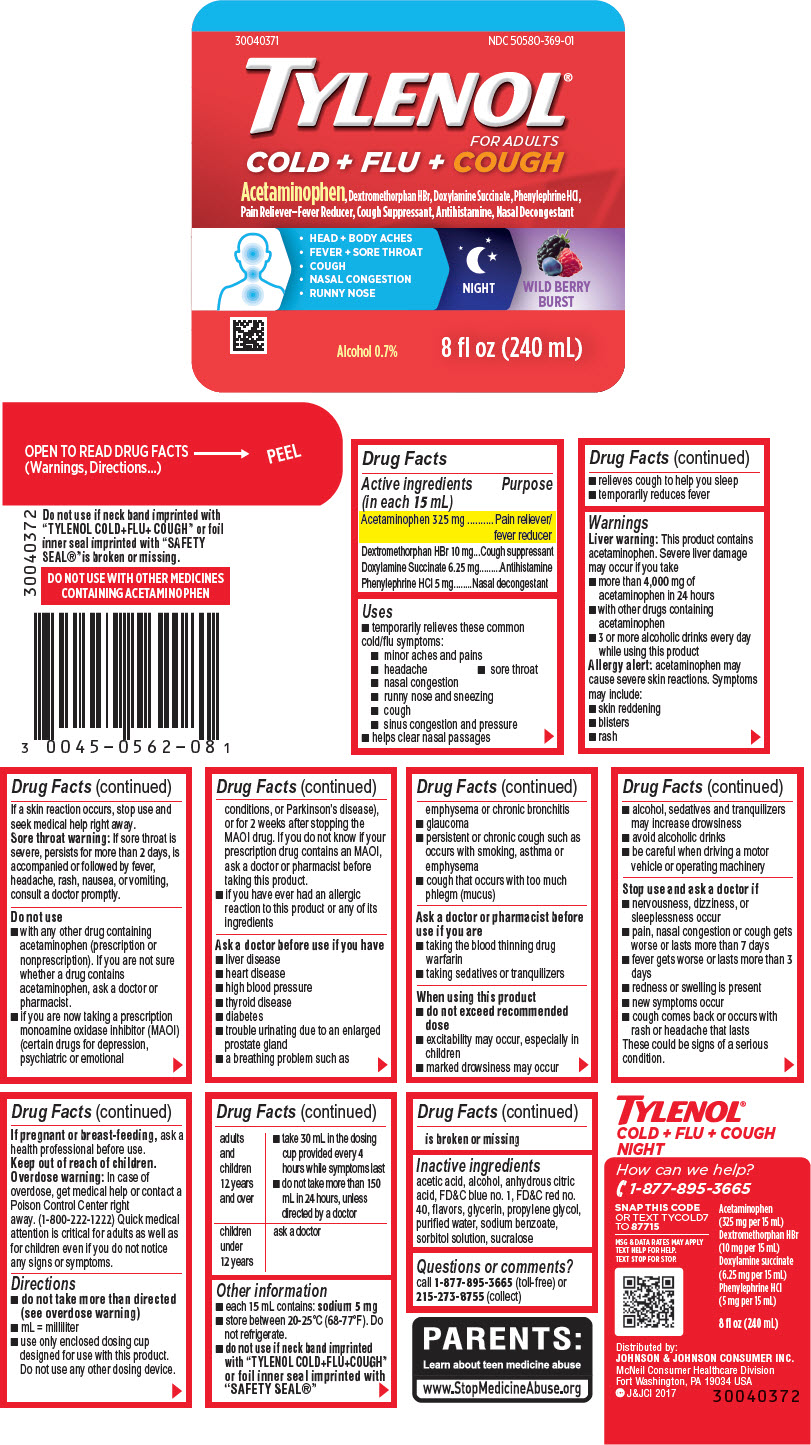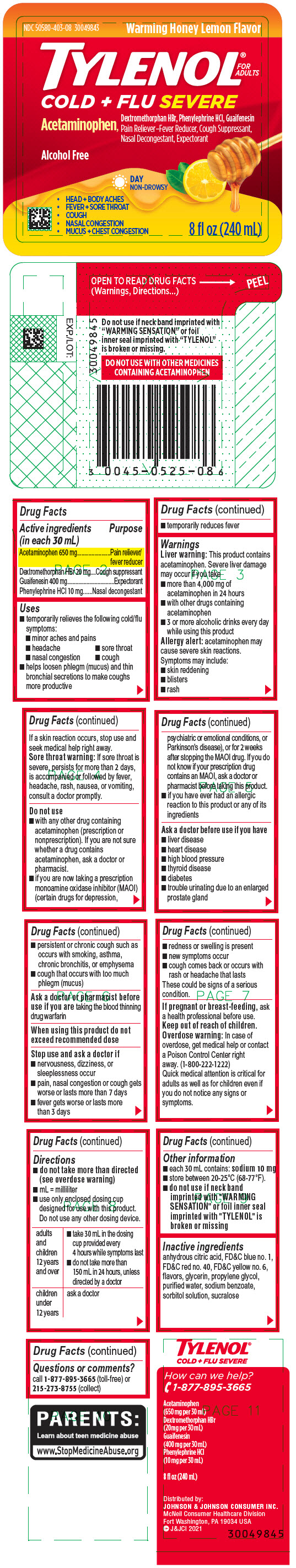 DRUG LABEL: Tylenol Cold Plus Flu Severe Day and Tylenol Cold Plus Flu Plus Cough Night 2-pack
NDC: 50580-526 | Form: KIT | Route: ORAL
Manufacturer: Kenvue Brands LLC
Category: otc | Type: HUMAN OTC DRUG LABEL
Date: 20250219

ACTIVE INGREDIENTS: ACETAMINOPHEN 325 mg/15 mL; DEXTROMETHORPHAN HYDROBROMIDE 10 mg/15 mL; DOXYLAMINE SUCCINATE 6.25 mg/15 mL; PHENYLEPHRINE HYDROCHLORIDE 5 mg/15 mL; ACETAMINOPHEN 650 mg/30 mL; DEXTROMETHORPHAN HYDROBROMIDE 20 mg/30 mL; GUAIFENESIN 400 mg/30 mL; PHENYLEPHRINE HYDROCHLORIDE 10 mg/30 mL
INACTIVE INGREDIENTS: ACETIC ACID; ALCOHOL; ANHYDROUS CITRIC ACID; FD&C BLUE NO. 1; FD&C RED NO. 40; GLYCERIN; PROPYLENE GLYCOL; WATER; SODIUM BENZOATE; SORBITOL SOLUTION; SUCRALOSE; FD&C BLUE NO. 1; FD&C RED NO. 40; FD&C YELLOW NO. 6; GLYCERIN; PROPYLENE GLYCOL; WATER; SODIUM BENZOATE; SORBITOL SOLUTION; SUCRALOSE; ANHYDROUS CITRIC ACID

Tylenol® Cold Plus Flu Severe Day and Tylenol Cold Plus Flu Plus Cough Night 2-pack

Tylenol® Cold plus Flu plus Cough
Night

Drug Facts

Active ingredients (in each 15 mL) Purpose
Acetaminophen 325 mg Pain reliever/ fever reducer
Dextromethorphan HBr 10 mg Cough suppressant
Doxylamine Succinate 6.25 mg Antihistamine
Phenylephrine HCl 5 mg Nasal decongestant

Active ingredients (in each 15 mL) | Purpose
Acetaminophen 325 mg | Pain reliever/ fever reducer
Dextromethorphan HBr 10 mg | Cough suppressant
Doxylamine Succinate 6.25 mg | Antihistamine
Phenylephrine HCl 5 mg | Nasal decongestant

Uses

- temporarily relieves these common cold/flu symptoms:
  - minor aches and pains
  - headache
  - sore throat
  - nasal congestion
  - runny nose and sneezing
  - cough
  - sinus congestion and pressure
- helps clear nasal passages
- relieves cough to help you sleep
- temporarily reduces fever

Warnings

Liver warning

This product contains acetaminophen. Severe liver damage may occur if you take

- more than 4,000 mg of acetaminophen in 24 hours
- with other drugs containing acetaminophen
- 3 or more alcoholic drinks every day while using this product

Allergy alert: acetaminophen may cause severe skin reactions. Symptoms may include:

- skin reddening
- blisters
- rash

If a skin reaction occurs, stop use and seek medical help right away.

Sore throat warning

If sore throat is severe, persists for more than 2 days, is accompanied or followed by fever, headache, rash, nausea, or vomiting, consult a doctor promptly.

Do not use

- with any other drug containing acetaminophen (prescription or nonprescription). If you are not sure whether a drug contains acetaminophen, ask a doctor or pharmacist.
- if you are now taking a prescription monoamine oxidase inhibitor (MAOI) (certain drugs for depression, psychiatric or emotional conditions, or Parkinson's disease), or for 2 weeks after stopping the MAOI drug. If you do not know if your prescription drug contains an MAOI, ask a doctor or pharmacist before taking this product.
- if you have ever had an allergic reaction to this product or any of its ingredients

Ask a doctor before use if you have

- liver disease
- heart disease
- high blood pressure
- thyroid disease
- diabetes
- trouble urinating due to an enlarged prostate gland
- a breathing problem such as emphysema or chronic bronchitis
- glaucoma
- persistent or chronic cough such as occurs with smoking, asthma or emphysema
- cough that occurs with too much phlegm (mucus)

Ask a doctor or pharmacist before use if you are

- taking the blood thinning drug warfarin
- taking sedatives or tranquilizers

When using this product

- do not exceed recommended dose
- excitability may occur, especially in children
- marked drowsiness may occur
- alcohol, sedatives and tranquilizers may increase drowsiness
- avoid alcoholic drinks
- be careful when driving a motor vehicle or operating machinery

Stop use and ask a doctor if

- nervousness, dizziness, or sleeplessness occur
- pain, nasal congestion or cough gets worse or lasts more than 7 days
- fever gets worse or lasts more than 3 days
- redness or swelling is present
- new symptoms occur
- cough comes back or occurs with rash or headache that lasts

These could be signs of a serious condition.

PREGNANCY OR BREAST FEEDING

If pregnant or breast-feeding, ask a health professional before use.

Keep out of reach of children.

Overdose warning

In case of overdose, get medical help or contact a Poison Control Center right away. (1-800-222-1222) Quick medical attention is critical for adults as well as for children even if you do not notice any signs or symptoms.

Directions

- do not take more than directed (see overdose warning)
- mL = milliliter
- use only enclosed dosing cup designed for use with this product. Do not use any other dosing device.

adults and children 12 years and over | - take 30 mL in the dosing cup provided every 4 hours while symptoms last - do not take more than 150 mL in 24 hours, unless directed by a doctor
children under 12 years | ask a doctor

Other information

- each 15 mL contains: sodium 5 mg
- store between 20-25°C (68-77°F).Do not refrigerate.
- do not use if neck band imprinted with TYLENOL COLD+FLU+COUGH” or foil inner seal imprinted with “SAFETY SEAL® is broken or missing.

Inactive ingredients

acetic acid, alcohol, anhydrous citric acid, FD&C blue no. 1, FD&C red no. 40, flavors, glycerin, propylene glycol, purified water, sodium benzoate, sorbitol solution, sucralose

Questions or comments?

call 1-877-895-3665 (toll-free) or 215-273-8755 (collect)

Tylenol® Cold plus Flu Severe

Drug Facts

Active ingredients (in each 30 mL) Purpose
Acetaminophen 650 mg Pain reliever/ fever reducer
Dextromethorphan HBr 20 mg Cough suppressant
Guaifenesin 400 mg Expectorant
Phenylephrine HCl 10 mg Nasal decongestant

Active ingredients (in each 30 mL) | Purpose
Acetaminophen 650 mg | Pain reliever/ fever reducer
Dextromethorphan HBr 20 mg | Cough suppressant
Guaifenesin 400 mg | Expectorant
Phenylephrine HCl 10 mg | Nasal decongestant

Uses

- temporarily relieves the following cold/flu symptoms:
  - minor aches and pains
  - headache
  - sore throat
  - nasal congestion
  - cough
- helps loosen phlegm (mucus) and thin bronchial secretions to make coughs more productive
- temporarily reduces fever

Warnings

Liver warning

This product contains acetaminophen. Severe liver damage may occur if you take

- more than 4,000 mg of acetaminophen in 24 hours
- with other drugs containing acetaminophen
- 3 or more alcoholic drinks every day while using this product

Allergy alert: acetaminophen may cause severe skin reactions. Symptoms may include:

- skin reddening
- blisters
- rash

If a skin reaction occurs, stop use and seek medical help right away.

Sore throat warning

If sore throat is severe, persists for more than 2 days, is accompanied or followed by fever, headache, rash, nausea, or vomiting, consult a doctor promptly.

Do not use

- with any other drug containing acetaminophen (prescription or nonprescription). If you are not sure whether a drug contains acetaminophen, ask a doctor or pharmacist.
- if you are now taking a prescription monoamine oxidase inhibitor (MAOI) (certain drugs for depression, psychiatric or emotional conditions, or Parkinson's disease), or for 2 weeks after stopping the MAOI drug. If you do not know if your prescription drug contains an MAOI, ask a doctor or pharmacist before taking this product.
- if you have ever had an allergic reaction to this product or any of its ingredients

Ask a doctor before use if you have

- liver disease
- heart disease
- high blood pressure
- thyroid disease
- diabetes
- trouble urinating due to an enlarged prostate gland
- persistent or chronic cough such as occurs with smoking, asthma, chronic bronchitis, or emphysema
- cough that occurs with too much phlegm (mucus)

Ask a doctor or pharmacist before use if you are taking the blood thinning drug warfarin

When using this product do not exceed recommended dose

Stop use and ask a doctor if

- nervousness, dizziness, or sleeplessness occur
- pain, nasal congestion or cough gets worse or lasts more than 7 days
- fever gets worse or lasts more than 3 days
- redness or swelling is present
- new symptoms occur
- cough comes back or occurs with rash or headache that lasts

These could be signs of a serious condition.

PREGNANCY OR BREAST FEEDING

If pregnant or breast-feeding, ask a health professional before use.

Keep out of reach of children.

Overdose warning

In case of overdose, get medical help or contact a Poison Control Center right away. (1-800-222-1222) Quick medical attention is critical for adults as well as for children even if you do not notice any signs or symptoms.

Directions

- do not take more than directed (see overdose warning)
- mL = milliliter
- use only enclosed dosing cup designed for use with this product. Do not use any other dosing device.

adults and children 12 years and over | - take 30 mL in the dosing cup provided every 4 hours while symptoms last - do not take more than 150 mL in 24 hours, unless directed by a doctor
children under 12 years | ask a doctor

Other information

- each 30 mL contains: sodium 10 mg
- store between 20-25°C (68-77°F).
- do not use if neck band imprinted with "WARMING SENSATION" or foil inner seal imprinted with "TYLENOL" is broken or missing.

Inactive ingredients

anhydrous citric acid, FD&C blue no. 1, FD&C red no. 40, FD&C yellow no. 6, flavors, glycerin, propylene glycol, purified water, sodium benzoate, sorbitol solution, sucralose

Questions or comments?

call 1-877-895-3665 (toll-free) or 215-273-8755 (collect)

PRINCIPAL DISPLAY PANEL

NDC 50580-526-01

DAYTIME
NIGHTTIME

PRINCIPAL DISPLAY PANEL

NDC 50580-369-01

TYLENOL®
FOR ADULTS
COLD + FLU + COUGH

Acetaminophen, Dextromethorphan HBr, Doxylamine Succinate, Phenylephrine HCl,
Pain Reliever–Fever Reducer, Cough Suppressant, Antihistamine, Nasal Decongestant

- HEAD + BODY ACHES
- FEVER + SORE THROAT
- COUGH
- NASAL CONGESTION
- RUNNY NOSE

NIGHT
WILD BERRY
BURST

Alcohol 0.7%
8 fl oz (240 mL)

PRINCIPAL DISPLAY PANEL

NDC 50580-403-08

30049843

Warming Honey Lemon Flavor

TYLENOL®
FOR ADULTS
COLD + FLU SEVERE

Acetaminophen, Dextromethorphan HBr, Phenylephrine HCl, Guaifenesin
Pain Reliever–Fever Reducer, Cough Suppressant, Nasal Decongestant, Expectorant

Alcohol Free

DAY
NON-DROWSY

- HEAD + BODY ACHES
- FEVER + SORE THROAT
- COUGH
- NASAL CONGESTION
- MUCUS + CHEST CONGESTION

8 fl oz (240 mL)